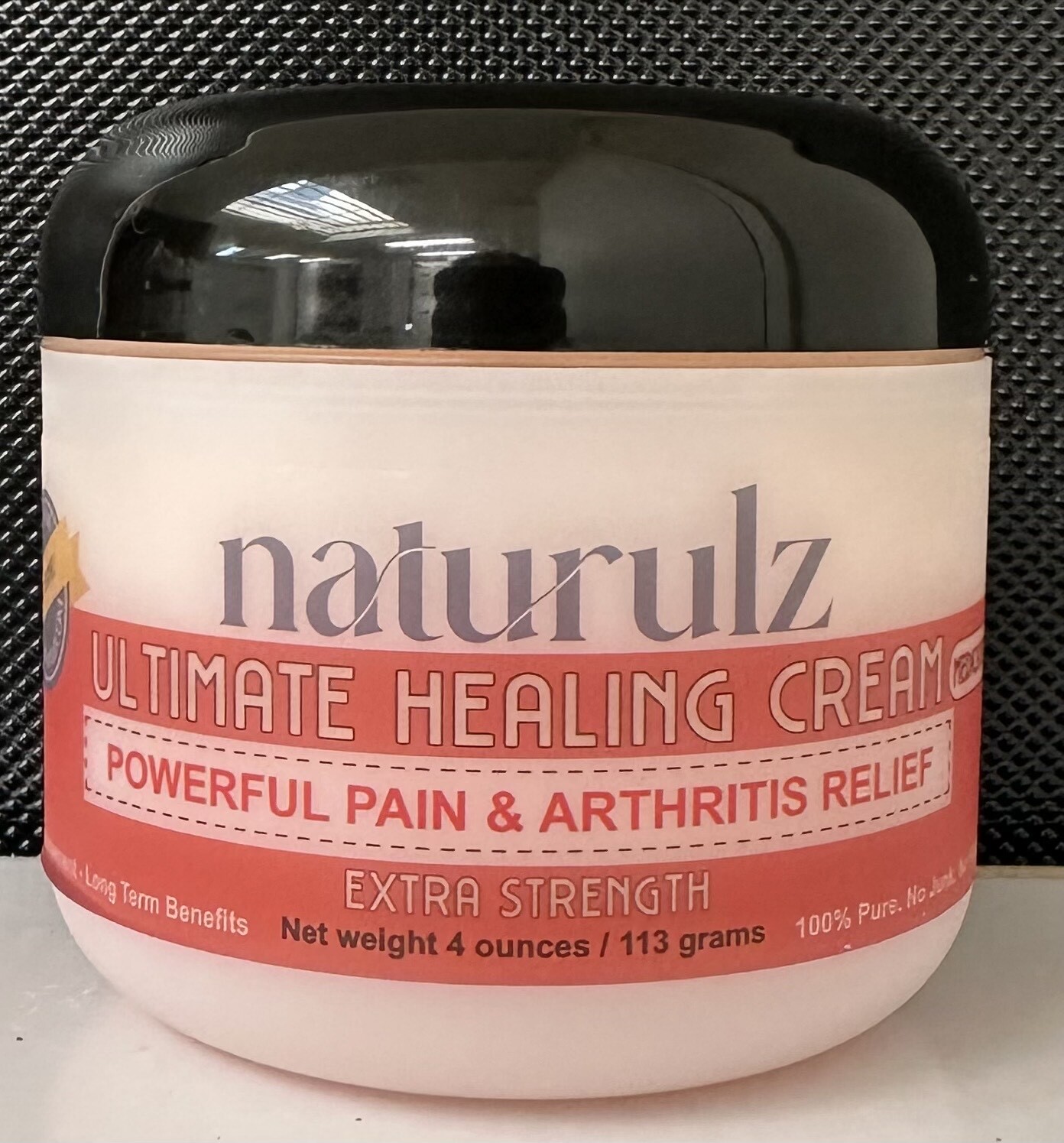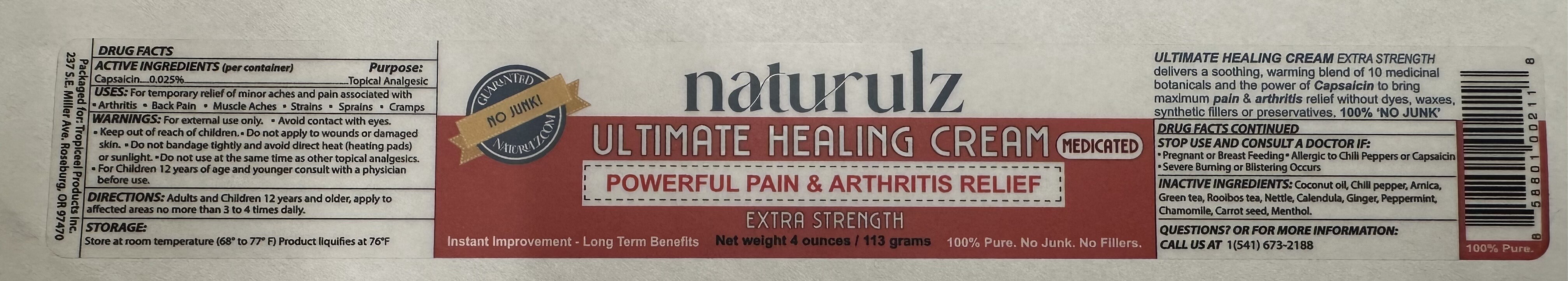 DRUG LABEL: NATURULZ ULTIMATE HEALING
NDC: 65112-100 | Form: CREAM
Manufacturer: I SHAY COSMETICS INC
Category: otc | Type: HUMAN OTC DRUG LABEL
Date: 20260203

ACTIVE INGREDIENTS: CAPSAICIN 0.025 g/100 g
INACTIVE INGREDIENTS: COCONUT OIL

ACTIVE INGREDIENT

Capsaicin 0.025%

PURPOSE

Topical Analgesic

USES

For temporary relief of minors aches and pain associated with Arthritis, Back Pain,Muscle Aches, Strains, Sprains, Cramps.

WARNINGS

For external use only. Avoid contact with eyes. Keep out of reach of children. Do not apply to wounds or damaged skin. Do not bandage tightly and avoid direct heat (heating pads) or sunlight. Do not use at the same time as other topical analgesics. For children 12 years of age and younger consult with a physician before use.

KEEP OUT OF REACH OF CHILDREN.

For Children 12 yearsof ge and younger consult with a physician before use.

DIRECTIONS

Adults and Children 12 years and older, apply to affected areas no more than 3 to 4 times daily.

STORAGE

Store at room temperature (68° to 77° F) Product liquifies at 76° F

STOP USE AND CONSULT A DOCTOR IF

Pregnant or Breast Feeding. Allergic to Chilli peppers or Capsaicin. Severe Burning or Blistering Occurs.

INACTIVE INGREDIENTS

Coconut oil, Chilli peppers, Arnica, Green tea, Rooibos tea, Nettle, Calendula,Ginger, Peppermint, Chamomile, Carrot seed, Menthol.

QUESTIONS? OR FOR MORE INFORMATION: CALL US AT

1(541) 673-2188